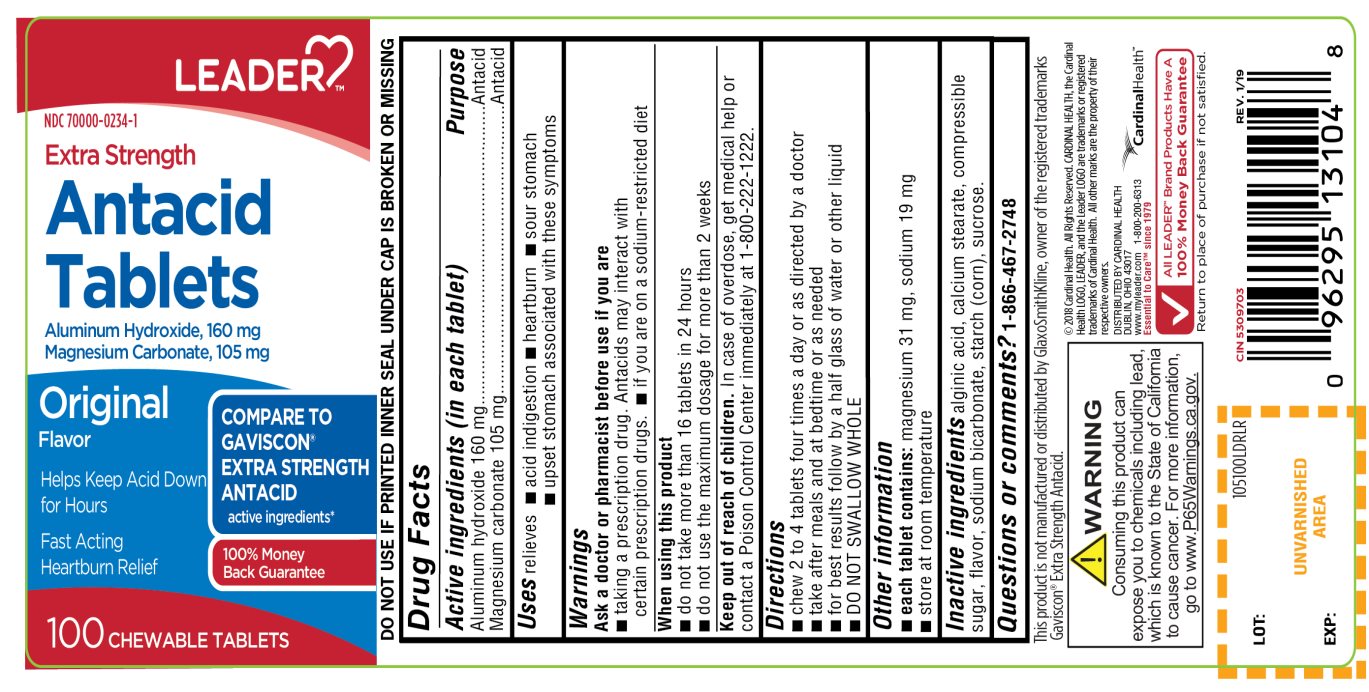 DRUG LABEL: Extra Strength Antacid

NDC: 70000-0234 | Form: TABLET, CHEWABLE
Manufacturer: Cardinal Health
Category: otc | Type: HUMAN OTC DRUG LABEL
Date: 20251014

ACTIVE INGREDIENTS: ALUMINUM HYDROXIDE 160 mg/1 1; MAGNESIUM CARBONATE 105 mg/1 1
INACTIVE INGREDIENTS: ALGINIC ACID; CALCIUM STEARATE; CORN SYRUP; SODIUM BICARBONATE; STARCH, CORN; SUCROSE

Cardinal Health Antacid Tablets Extra Strength Original Flavor

Active ingredients (in each tablet)

Aluminum hydroxide 160 mg

Magnesium carbonate 105 mg

Purpose

Antacid

Antacid

Uses

relieves

- acid indigestion
- heartburn
- sour stomach
- upset stomach associated with these symptoms

Warnings

Consuming this product can expose you to chemicals including lead, which is known to the State of California to cause cancer. For more information, go to www.P65Warningd.ca.gov

Ask a doctor or pharmacist before use if you are

- taking a prescription drug. Antacids may interact with certain prescription drugs
- If you are on a sodium-restricted diet

When using this product

- do not take more than 16 tablets in 24 hours
- do not use the maximum dosage for more than 2 weeks

Keep out of reach of children.

In case of overdose, get medical help or contact a Poison Control Center immediately.

1-800-222-1222

Directions

- chew 2 to 4 tablets four times a day or as directed by a doctor
- take after meals and at bedtime or as needed
- for best results follow by a half glass of water or other liquid
- DO NOT SWALLOW WHOLE

Other information

- Each tablet contains:magnesium 31 mg, sodium 19 mg
- Store at room temperature.

Inactive ingredients

alginic acid, calcium stearate, compressible sugar, flavor, sodium bicarbonate, starch (corn), sucrose.

Principal Display Panel

LEADER™

NDC 70000-0234-1

COMPARE TO GAVISCON® EXTRA STRENGTH ANTACID active ingredients*

Extra Strength

Antacid Tablets

Aluminum Hydroxide, 160 mg

Magnesium Carbonate, 105 mg

Original Flavor

- Helps Keep Acid Down for Hours
- Fast-Acting Heartburn Relief

100 Chewable Tablets

100% Money Back Guarantee

- DO NOT USE IF PRINTED INNER SEAL UNDER CAP IS BROKEN OR MISSING

©2018 Cardinal Health. All Right Reserved. CARDINAL HEALTH, the Cardinal Health LOGO, LEADER and the Leader LOGO are trademarks or registered

trademarks of Cardinal Health. All other marks are the property of their respective owners.

DISTRIBUTED BY CARDINAL HEALTH

DUBLIN, OHIO 43017

www.myleader.com1-800-200-6313

All LEADER™ Brand Products Have A 100% Money Back Guarantee. Return to place of purchase if not satisfied.

This product is not manufactured or distributed by GlaxoSmithKline, owner of the registered trademarks of Gaviscon®Extra Strength Antacid.